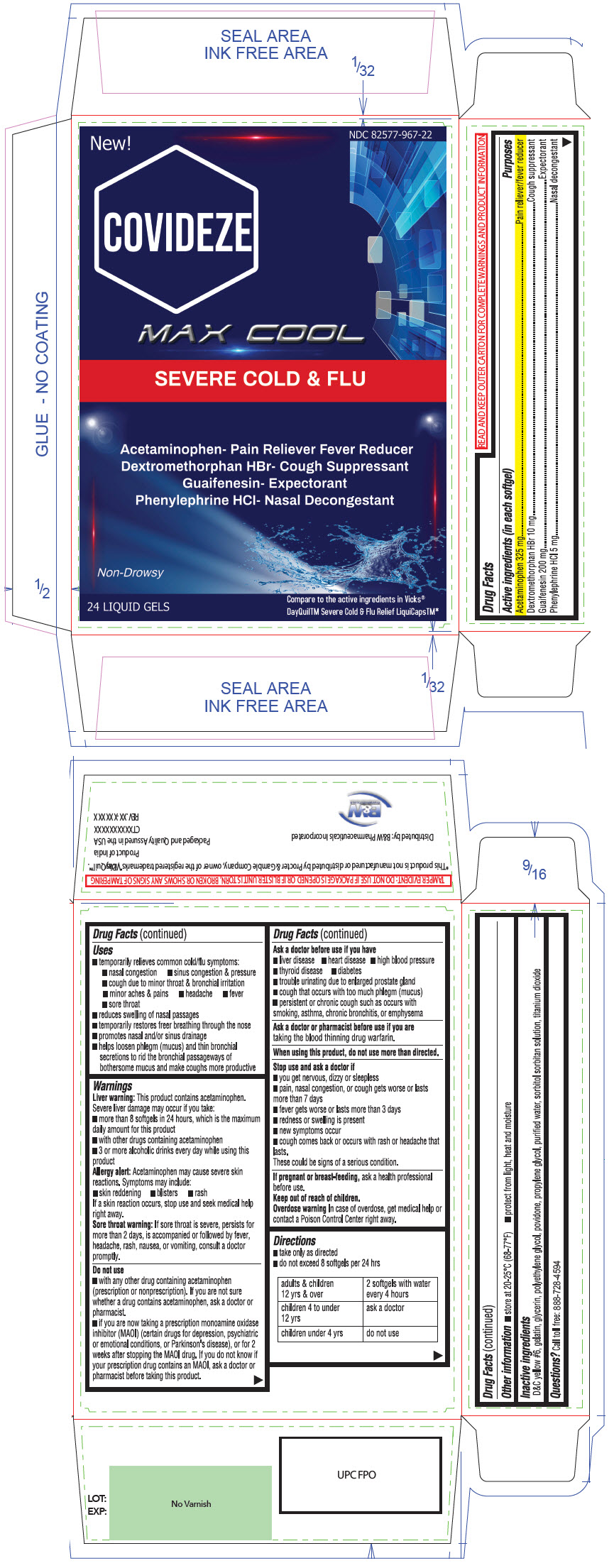 DRUG LABEL: Covideze
NDC: 82577-967 | Form: CAPSULE, LIQUID FILLED
Manufacturer: B&W Pharmaceuticals Inc.
Category: otc | Type: HUMAN OTC DRUG LABEL
Date: 20220323

ACTIVE INGREDIENTS: Acetaminophen 325 mg/1 1; Dextromethorphan Hydrobromide 10 mg/1 1; Guaifenesin 200 mg/1 1; Phenylephrine Hydrochloride 5 mg/1 1
INACTIVE INGREDIENTS: FD&C YELLOW NO. 6; GELATIN, UNSPECIFIED; Glycerin; POLYETHYLENE GLYCOL, UNSPECIFIED; POVIDONE, UNSPECIFIED; PROPYLENE GLYCOL; Water; Titanium Dioxide

Covideze

Drug Facts

ACTIVE INGREDIENT

PURPOSE

Active ingredients (in each softgel) | Purposes
Acetaminophen 325 mg | Pain reliever/fever reducer
Dextromethorphan HBr 10 mg | Cough suppressant
Guaifenesin 200 mg | Expectorant
Phenylephrine HCl 5 mg | Nasal decongestant

Uses

- temporarily relieves common cold/flu symptoms:
- nasal congestion
- sinus congestion & pressure
- cough due to minor throat & bronchial irritation
- minor aches & pains
- headache
- fever
- sore throat
- reduces swelling of nasal passages
- temporarily restores freer breathing through the nose
- promotes nasal and/or sinus drainage
- helps loosen phlegm (mucus) and thin bronchial secretions to rid the bronchial passageways of bothersome mucus and make coughs more productive.

Warnings

Liver warning

This product contains acetaminophen.

Severe liver damage may occur if you take:

- more than 8 softgels in 24 hours, which is the maximum daily amount for this product
- with other drugs containing acetaminophen
- 3 or more alcoholic drinks every day while using this product

Allergy Alert

Acetaminophen may cause severe skin reactions. Symptoms may include:

- Skin reddening
- Blisters
- Rash

If a skin reaction occurs, stop use and seek medical help right away.

Sore throat warning

If sore throat is severe, persists for more than 2 days, is accompanied or followed by fever, headache, rash, nausea, or vomiting, consult a doctor promptly.

Do not use

- with any other drug containing acetaminophen (prescription or nonprescription). If you are not sure whether a drug contains acetaminophen, ask a doctor or pharmacist.
- if you are now taking a prescription monoamine oxidase inhibitor (MAOI) (certain drugs for depression, psychiatric or emotional conditions, or Parkinson's disease), or for 2 weeks after stopping the MAOI drug. If you do not know if your prescription drug contains an MAOI, ask a doctor or pharmacist before taking this product.

Ask a doctor before use if you have

- liver disease
- heart disease
- high blood pressure
- thyroid disease
- diabetes
- trouble urinating due to enlarged prostate gland
- cough that occurs with too much phlegm (mucus)
- persistent or chronic cough such as occurs with smoking, asthma, chronic
- bronchitis, or emphysema

Ask a doctor or pharmacist before use if you are taking the blood thinning drug warfarin.

When using this product, do not use more than directed.

Stop use and ask a doctor if

- you get nervous, dizzy or sleepless
- pain, nasal congestion or cough get worse or last more than 7 days
- fever gets worse or lasts more than 3 days
- redness or swelling is present
- new symptoms occur
- cough comes back or occurs with rash or headache that lasts.

These could be signs of a serious condition.

PREGNANCY OR BREAST FEEDING

If pregnant or breast-feeding, ask a health professional before use.

Keep out of reach of children.

Overdose warning

In case of overdose, get medical help or contact a Poison Control Center right away.

Directions

- take only as directed
- do not exceed 8 softgels per 24 hrs

adults & children 12 yrs & over | 2 softgels with water every 4 hours
children 4 to under 12 yrs | ask a doctor
children under 4 yrs | do not use

Other information

- Store at 20-25°C (68-77°F)
- Protect from light, heat and moisture

Inactive ingredients

D&C yellow #6, gelatin, glycerin, polyethylene glycol, povidone, propylene glycol, purified water, sorbitol sorbitan solution, titanium dioxide

Questions?

Call toll free: 888-728-4594

Distributed by: B&W Pharmaceuticals Incorporated

PRINCIPAL DISPLAY PANEL - 24 Liquid Gel Blister Pack Carton

New!
NDC 82577-967-22

COVIDEZE

MAX COOL

SEVERE COLD & FLU

Acetaminophen- Pain Reliever Fever Reducer
Dextromethorphan HBr- Cough Suppressant
Guaifenesin- Expectorant
Phenylephrine HCl- Nasal Decongestant

Non-Drowsy

24 LIQUID GELS

Compare to the active ingredients in Vicks®
DayQuilTM Severe Cold & Flu Relief LiquiCapsTM*